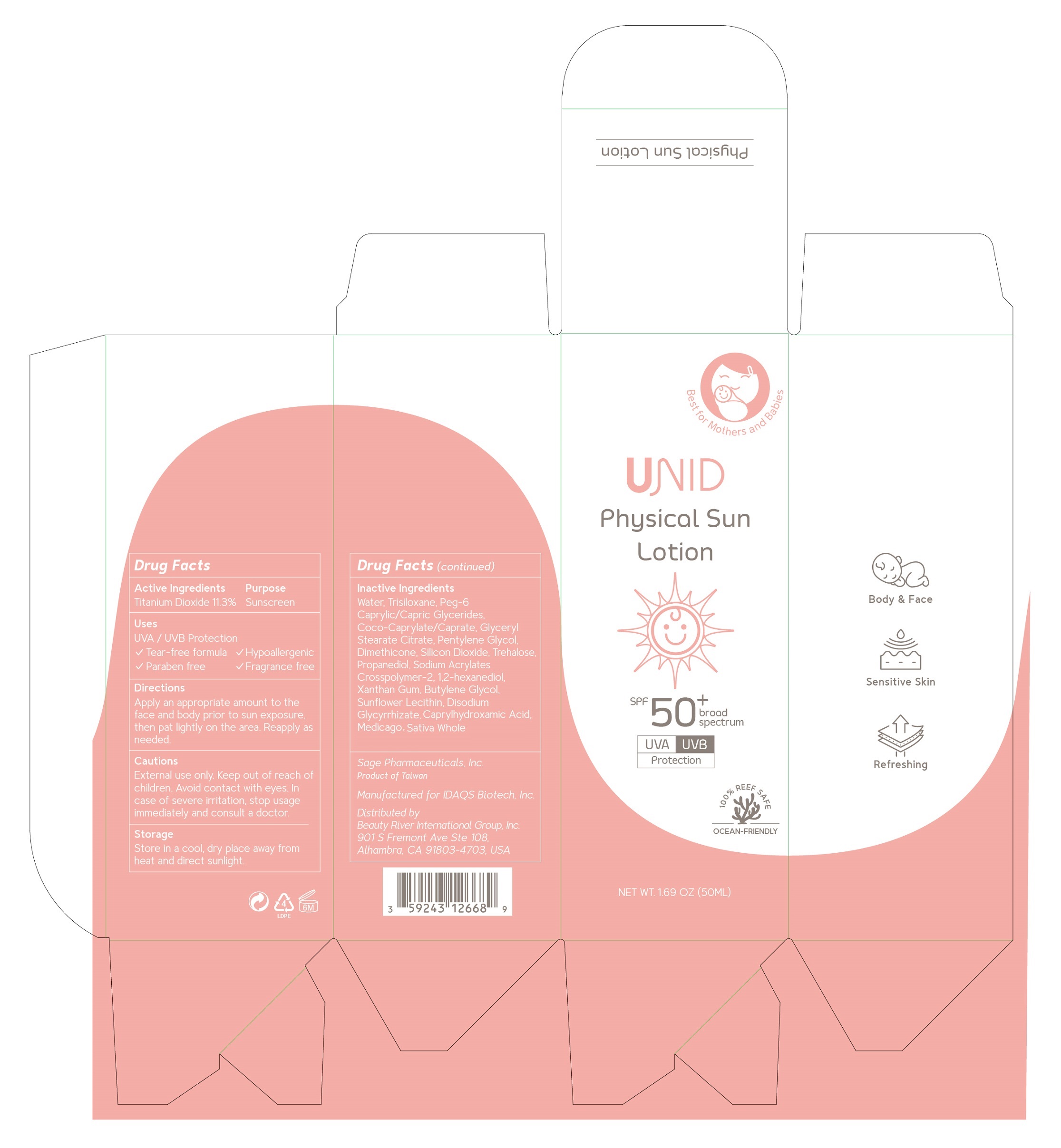 DRUG LABEL: UNID Physical Sun
NDC: 83119-243 | Form: LOTION
Manufacturer: Sage Pharmaceuticals Inc
Category: otc | Type: HUMAN OTC DRUG LABEL
Date: 20251003

ACTIVE INGREDIENTS: TITANIUM DIOXIDE 11.3 g/100 mL
INACTIVE INGREDIENTS: WATER; TRISILOXANE; PEG-6 CAPRYLIC/CAPRIC GLYCERIDES; COCO-CAPRYLATE/CAPRATE; GLYCERYL STEARATE CITRATE; PENTYLENE GLYCOL; DIMETHICONE; SILICON DIOXIDE; TREHALOSE; PROPANEDIOL; SODIUM ACRYLATES CROSSPOLYMER-2; 1,2-HEXANEDIOL; XANTHAN GUM; BUTYLENE GLYCOL; LECITHIN, SUNFLOWER; DISODIUM GLYCYRRHIZATE; CAPRYLHYDROXAMIC ACID; MEDICAGO SATIVA WHOLE

Sage Pharmaceuticals Inc

Active Ingredients

Titanium Dioxide 11.3%

Purpose

Sunscreen

Uses

HVA / UVB protection

- Tear-free formula
- Paraben free
- Hypoallergenic
- Fragrance free

Directions

Apply an appropriate amount to the face and body prior to sun exposure, then pat lightly on the area. Reapply as needed.

Cautions

External use only

Keep out of reach of children.

STOP USE

Avoid contact with eyes. In case of severe irritation, stop usage immediately and consult a doctor.

Storage

Store in a cool, dry place away from heat and direct sunlight.

Sage Pharmaceuticals Inc

Product of Taiwan

Manufactured for IDAQS Biotech, Inc.

Distributed by Beauty River International Inc.
901 S. Fremont Ave 108, Alhambra, CA 91803-4703, USA

Inactive Ingredients

WATER, TRISILOXANE, PEG-6 CAPRYLIC/CAPRIC GLYCERIDES, COCO-CAPRYLATE/CAPRATE, GLYCERYL STEARATE CITRATE, PENTYLENE GLYCOL,
DIMETHICONE, SILICON DIOXIDE, TREHALOSE, PROPANEDIOL, SODIUM ACRYLATES CROSSPOLYMER-2, 1,2-HEXANEDIOL, XANTHAN GUM, BUTYLENE GLYCOL, LECITHIN, SUNFLOWER, DISODIUM GLYCYRRHIZATE, CAPRYLHYDROXAMIC ACID, MEDICAGO SATIVA WHOLE